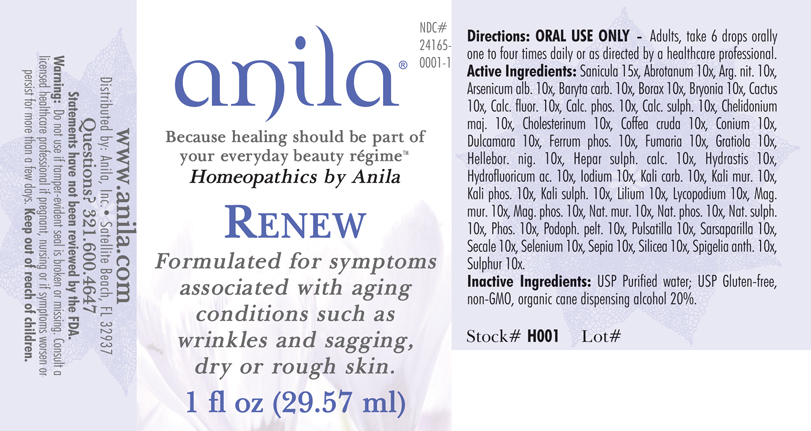 DRUG LABEL: Renew 
NDC: 24165-0001 | Form: LIQUID
Manufacturer: Anila, Inc.
Category: homeopathic | Type: HUMAN OTC DRUG LABEL
Date: 20140415

ACTIVE INGREDIENTS: Calcium Chloride 15 [hp_X]/1 mL; Calcium Bicarbonate 15 [hp_X]/1 mL; Potassium Sulfate 15 [hp_X]/1 mL; Sodium Bicarbonate 15 [hp_X]/1 mL; Artemisia Abrotanum Flowering Top 10 [hp_X]/1 mL; Silver Nitrate 10 [hp_X]/1 mL; Arsenic Trioxide 10 [hp_X]/1 mL; Barium Carbonate 10 [hp_X]/1 mL; Sodium Borate 10 [hp_X]/1 mL; Bryonia Alba Root 10 [hp_X]/1 mL; Selenicereus Grandiflorus Stem 10 [hp_X]/1 mL; Calcium Fluoride 10 [hp_X]/1 mL; Tribasic Calcium Phosphate 10 [hp_X]/1 mL; Calcium Sulfate Anhydrous 10 [hp_X]/1 mL; Chelidonium Majus 10 [hp_X]/1 mL; Cholesterol 10 [hp_X]/1 mL; Arabica Coffee Bean 10 [hp_X]/1 mL; Conium Maculatum Flowering Top 10 [hp_X]/1 mL; Solanum Dulcamara Top 10 [hp_X]/1 mL; Ferrosoferric Phosphate 10 [hp_X]/1 mL; Hydrofluoric Acid 10 [hp_X]/1 mL; Fumaria Officinalis Flowering Top 10 [hp_X]/1 mL; Gratiola Officinalis 10 [hp_X]/1 mL; Helleborus Niger Root 10 [hp_X]/1 mL; Calcium Sulfide 10 [hp_X]/1 mL; Goldenseal 10 [hp_X]/1 mL; Iodine 10 [hp_X]/1 mL; Potassium Carbonate 10 [hp_X]/1 mL; Potassium Chloride 10 [hp_X]/1 mL; Potassium Phosphate, Dibasic 10 [hp_X]/1 mL; Lilium Lancifolium Whole Flowering 10 [hp_X]/1 mL; Lycopodium Clavatum Spore 10 [hp_X]/1 mL; Magnesium Chloride 10 [hp_X]/1 mL; Magnesium Phosphate, Dibasic Trihydrate 10 [hp_X]/1 mL; Sodium Chloride 10 [hp_X]/1 mL; Sodium Phosphate, Dibasic, Heptahydrate 10 [hp_X]/1 mL; Sodium Sulfate 10 [hp_X]/1 mL; Phosphorus 10 [hp_X]/1 mL; Podophyllum 10 [hp_X]/1 mL; Pulsatilla Vulgaris 10 [hp_X]/1 mL; Smilax Regelii Root 10 [hp_X]/1 mL; Claviceps Purpurea Sclerotium 10 [hp_X]/1 mL; Selenium 10 [hp_X]/1 mL; Sepia Officinalis Juice 10 [hp_X]/1 mL; Silicon Dioxide 10 [hp_X]/1 mL; Spigelia Anthelmia 10 [hp_X]/1 mL; Sulfur 10 [hp_X]/1 mL
INACTIVE INGREDIENTS: Alcohol

Renew

INDICATIONS & USAGE SECTION

Renew Formulated for symptoms associated with aging conditions such as wrinkles and sagging, dry or rough skin.

DOSAGE & ADMINISTRATION SECTION

Directions: ORAL USE ONLY - SHAKE WELL. Ages 12 and up, take 6 drops orally one to four times or as directed by a healthcare professional.

OTC - ACTIVE INGREDIENT SECTION

Sanicula 15x, Abrotanum 10x, Arg. nit. 10x, Arsenicum alb. 10x, Baryta carb. 10x, Borax 10x, Bryonia 10x, Cactus 10x, Calc. fluor. 10x, Calc. phos. 10x, Calc. sulph. 10x, Chelidonium maj. 10x, Cholesterinum 10x, Coffea cruda 10x, Conium 10x, Dulcamara 10x, Ferrum phos. 10x, Fumaria 10x, Gratiola 10x, Hellebor. nig. 10x, Hepar sulph. calc. 10x, Hydrastis 10x, Hydrofluoricum ac. 10x, Iodium 10x, Kali carb. 10x, Kali mur. 10x, Kali phos. 10x, Kali sulph. 10x, Lilium 10x, Lycopodium 10x, Mag. mur. 10x, Mag. phos. 10x, Nat. mur.10x, Nat.phos. 10x, Nat. sulph. 10x, Phos. 10x, Podoph. pelt. 10x, Pulsatilla 10x, Sarsaparilla 10x, Secale 10x, Selenium 10x, Sepia 10x, Silicea 10x, Spigelia anth. 10x, Sulphur 10x.

OTC - PURPOSE SECTION

Formulated for symptoms associated with aging conditions such as wrinkles and sagging, dry or rough skin.

INACTIVE INGREDIENT SECTION

Inactive Ingredients: USP Purified Water; USP Gluten-free, non-GMO, organic cane dispensing alcohol 20%.

QUESTIONS SECTION

www.anila.com: Anila, Inc., Satellite Beach, FL 32937 Questions? 1.321.600.4647

WARNINGS SECTION

Warning: Do not use if tamper - evident seal is broken or missing. Consult a licensed healthcare professional if pregnant, nursing or if symptoms worsen or persist for more than a few days. Keep out of reach of children.

OTC - PREGNANCY OR BREAST FEEDING SECTION

Consult a licensed healthcare professional if pregnant, nursing or if symptoms worsen or persist for more than a few days.

OTC - KEEP OUT OF REACH OF CHILDREN SECTION

Keep out of reach of children.